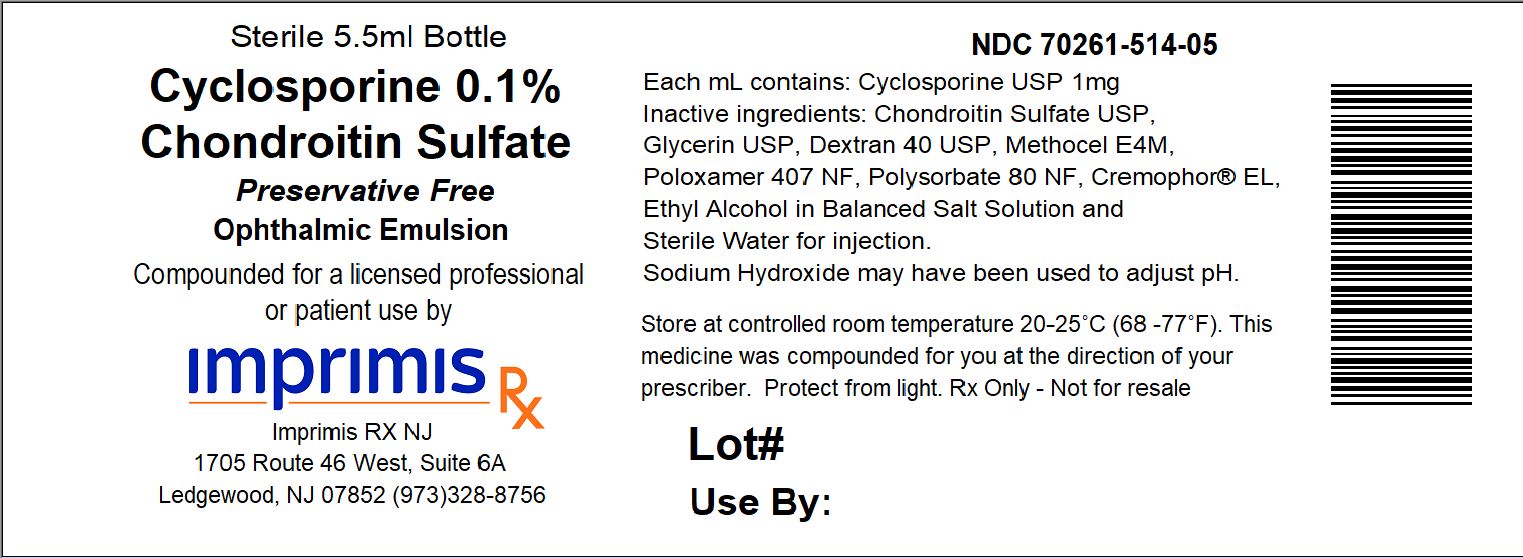 DRUG LABEL: Cyclosporine/Chondroitin Sulfate PF
NDC: 70261-514 | Form: EMULSION
Manufacturer: ImprimisRx NJ
Category: prescription | Type: HUMAN PRESCRIPTION DRUG LABEL
Date: 20180226

ACTIVE INGREDIENTS: CYCLOSPORINE 1 mg/1 mL

STORAGE AND HANDLING

Store at 20° to 25° C (68° to 77° F)